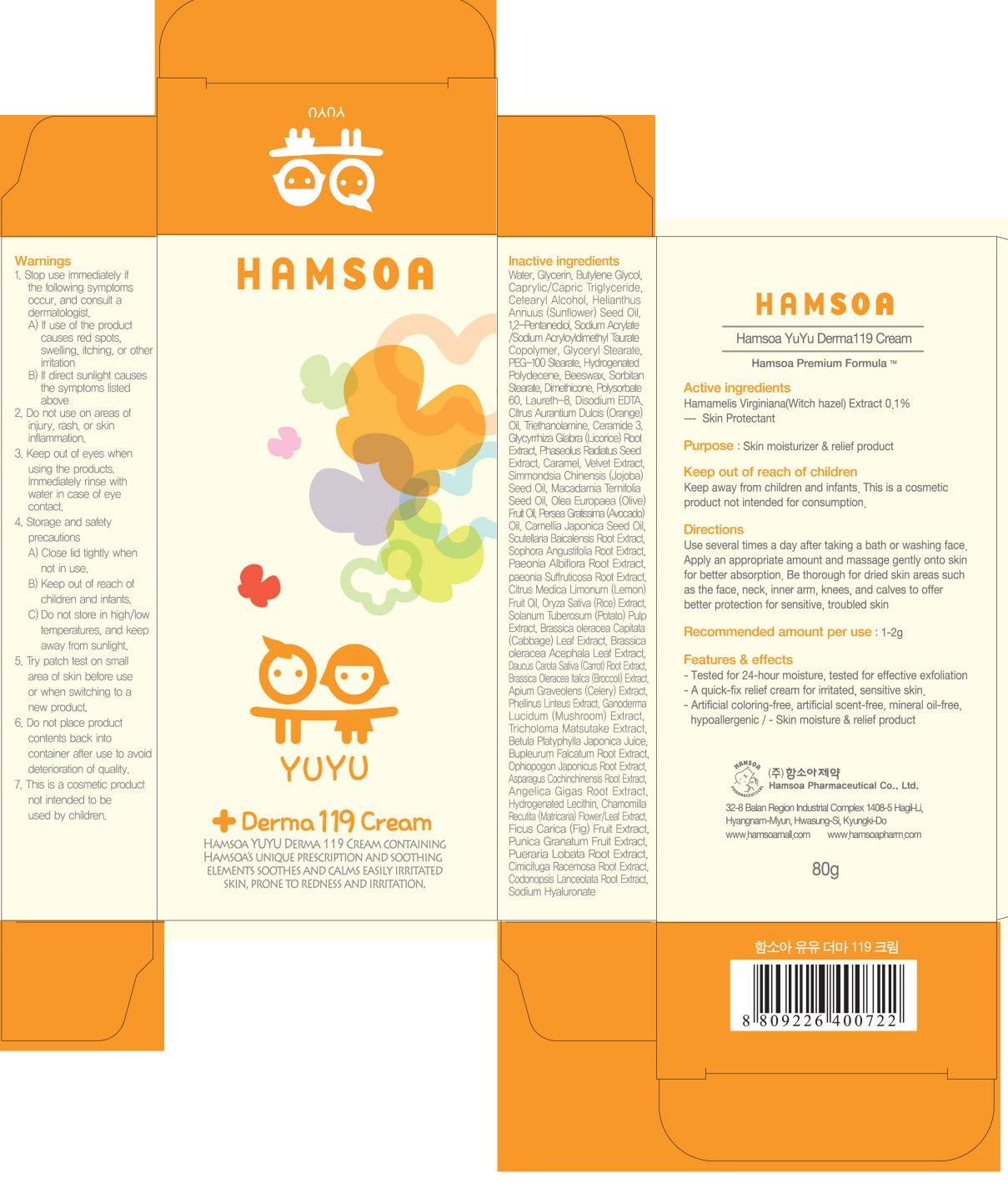 DRUG LABEL: HAMSOA YUYU DERMA119
NDC: 50964-070 | Form: CREAM
Manufacturer: HAMSOA PHARMACEUTICAL CO., LTD.
Category: otc | Type: HUMAN OTC DRUG LABEL
Date: 20120822

ACTIVE INGREDIENTS: WITCH HAZEL 0.08 g/80 g
INACTIVE INGREDIENTS: WATER; GLYCERIN; BUTYLENE GLYCOL; MEDIUM-CHAIN TRIGLYCERIDES; CETOSTEARYL ALCOHOL; SUNFLOWER OIL

ACTIVE INGREDIENT

Active ingredient: Witch hazel(Hamamelis Virginiana) 0.1%

INACTIVE INGREDIENT

Inactive ingredients:
Water, Glycerin, Butylene Glycol, Caprylic/Capric Triglyceride, Cetearyl Alcohol, Helianthus Annuus (Sunflower) Seed Oil, 1,2-Pentanediol,
Sodium Acrylate/Sodium Acryloyldimethyl Taurate Copolymer, Glyceryl Stearate, PEG-100 Stearate, Hydrogenated Polydecene, Beeswax,
Sorbitan Stearate, Dimethicone, Polysorbate 60, Laureth-8, Disodium EDTA, Citrus Aurantium Dulcis (Orange) Oil, Triethanolamine, Ceramide 3, Glycyrrhiza Glabra (Licorice) Root Extract, Phaseolus Radiatus Seed Extract, Caramel, Velvet Extract, Simmondsia Chinensis (Jojoba) Seed Oil, Macadamia Ternifolia Seed Oil, Olea Europaea (Olive) Fruit Oil, Persea Gratissima (Avocado) Oil, Camellia Japonica Seed Oil, Scutellaria Baicalensis Root Extract, Sophora Angustifolia Root Extract, Paeonia Albiflora Root Extract, paeonia Suffruticosa Root Extract, Citrus Medica Limonum (Lemon) Fruit Oil, Oryza Sativa (Rice) Extract, Solanum Tuberosum (Potato) Pulp Extract, Brassica oleracea Capitata (Cabbage) Leaf Extract, Brassica oleracea Acephala Leaf Extract, Daucus Carota Sativa (Carrot) Root Extract, Brassica Oleracea Italica (Broccoli) Extract, Apium Graveolens (Celery) Extract, Phellinus Linteus Extract, Ganoderma Lucidum (Mushroom) Extract, Tricholoma Matsutake Extract, Betula Platyphylla Japonica Juice, Bupleurum Falcatum Root Extract, Ophiopogon Japonicus Root Extract, Asparagus Cochinchinensis Root Extract, Angelica Gigas Root Extract, Hydrogenated Lecithin, Chamomilla Recutita (Matricaria) Flower/Leaf Extract,
Ficus Carica (Fig) Fruit Extract, Punica Granatum Fruit Extract, Pueraria Lobata Root Extract, Cimicifuga Racemosa Root Extract,
Codonopsis Lanceolata Root Extract, Sodium Hyaluronate

PURPOSE

Purpose: Skin moisturizer

WARNINGS

1. Stop use immediately if the following symptoms occur, and consult a dermatologist.
A) If use of the product causes red spots, swelling, itching, or other irritation
B) If direct sunlight causes the symptoms listed above
2. Do not use on areas of injury, rash, or skin inflammation.
3. Keep out of eyes when using the products. Immediately rinse with water in case of eye contact.
4. Storage and safety precautions
A) Close lid tightly when not in use.
B) Keep out of reach of children and infants.
C)Do not store in high/low temperatures, and keep away from sunlight.
5. Try patch test on small area of skin before use or when switching to a new product.
6. Do not place product contents back into container after use to avoid deterioration of quality.
7. This is a cosmetic product not intended to be used by children

KEEP OUT OF REACH OF CHILDREN

Keep away from children and infants.
This is a cosmetic product not intended for consumption.

INDICATIONS AND USAGE

Directions:
Use several times a day after taking a bath or washing face.
Apply an appropriate amount and massage gently onto skin for better absorption.
Be thorough for dried skin areas such as the face, neck, inner arm, knees, and calves to offer better protection for sensitive, troubled skin.

DOSAGE AND ADMINISTRATION

Recommended amount per use: 1-2g